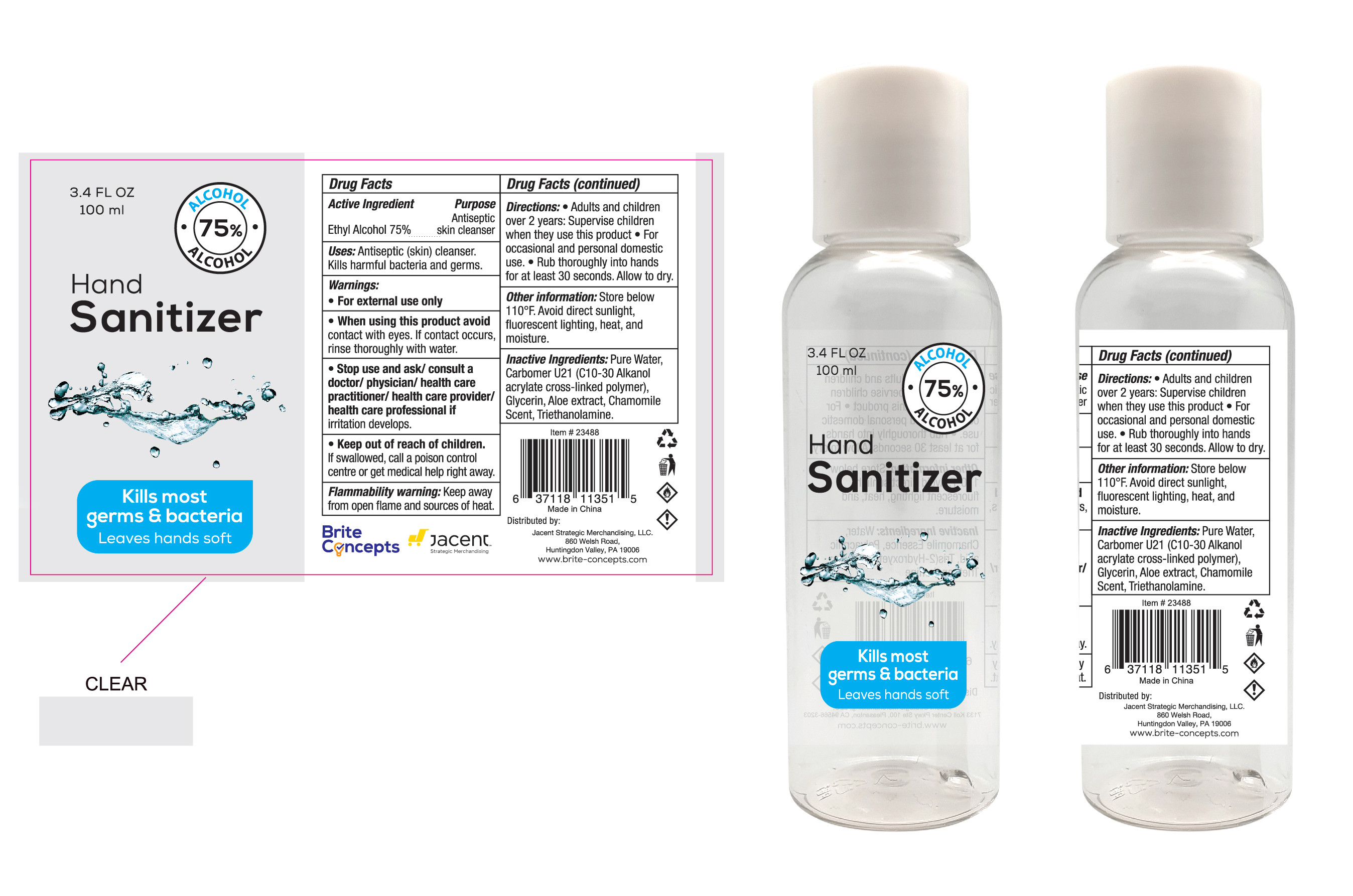 DRUG LABEL: Hand Sanitizer
NDC: 59004-011 | Form: GEL
Manufacturer: JACENT STRATEGIC MERCHANDISING, LLC
Category: otc | Type: HUMAN OTC DRUG LABEL
Date: 20200804

ACTIVE INGREDIENTS: ALCOHOL 75 mL/100 mL
INACTIVE INGREDIENTS: WATER; CARBOMER HOMOPOLYMER, UNSPECIFIED TYPE; CHAMOMILE; GLYCERIN; ALOE; TROLAMINE

DOSAGE AND ADMINISTRATION

Store below 110°F Avoid direct sunlight,fluorescent lighting, heat, and moisture.

INACTIVE INGREDIENT

Pure Water, Carbomer U21 (C10-30 Alkanol acrylate cros-inked polymer), Glycerin, Aloe extract,Chamomile Scent, Triethanolamine.

INDICATIONS AND USAGE

1.Adults and children over 2 years: Supervise children when they use this product

2.For occasional and personal domestic use.

3.Rub thoroughly into hands for at least 30 seconds. Allow to dry.

ACTIVE INGREDIENT

Ethyl Alcohol

keep out of reach of children

PURPOSE

Disinfection
Sterilization

WARNINGS

1.For external use only
2.When using this product avoid contact with eyes. If contact occurs, rinse thoroughly with water.
3.Stop use and ask / consult a doctor / physician 1 health care practitioner I health care provider/ health care professional if iritation develops.
4.Keep out of reach of children.If swallowed, call a poison control centre or get medical help right away,